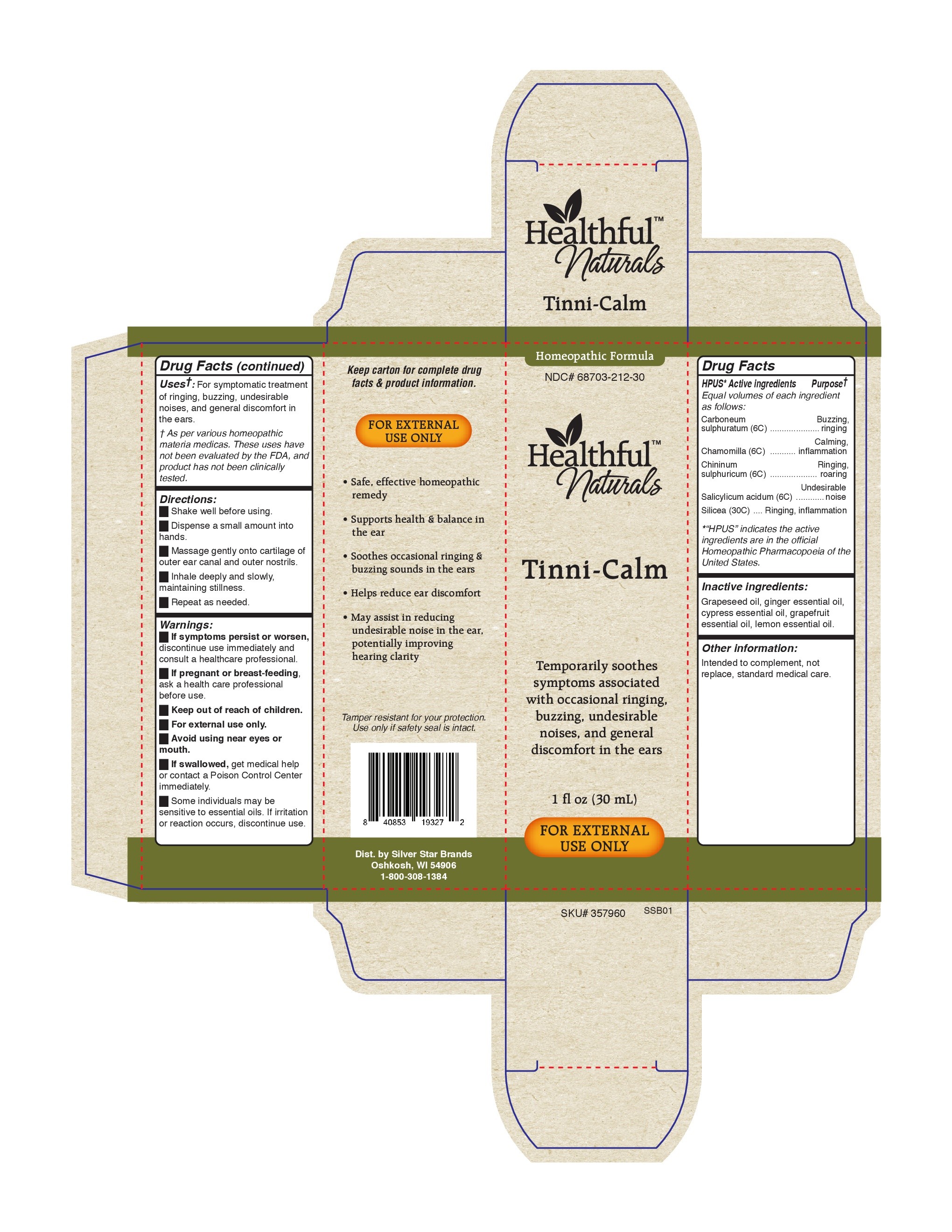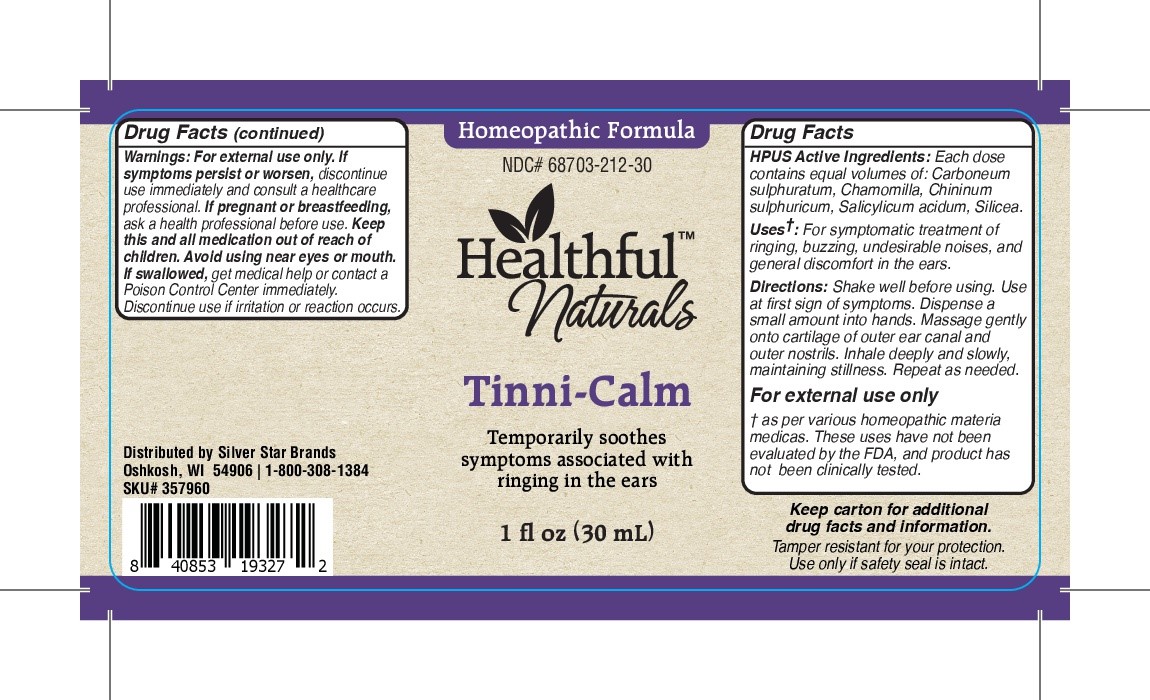 DRUG LABEL: Tinni-Calm
NDC: 68703-212 | Form: OIL
Manufacturer: Silver Star Brands
Category: homeopathic | Type: HUMAN OTC DRUG LABEL
Date: 20201210

ACTIVE INGREDIENTS: CARBON DISULFIDE 6 [hp_C]/30 mL; SILICON DIOXIDE 30 [hp_C]/30 mL; HYDROQUININE SULFATE 6 [hp_C]/30 mL; MAGNESIUM SALICYLATE 6 [hp_C]/30 mL; MATRICARIA CHAMOMILLA FLOWERING TOP OIL 6 [hp_C]/30 mL
INACTIVE INGREDIENTS: GRAPEFRUIT; LEMON OIL; GRAPE SEED OIL; GINGER OIL

Healthful™ Naturals Tinni-Calm

HPUS Active Ingredients: Each does contains equal volumes of: Carboneum sulphuratum, Chamomilla, Chininum sulphuricum, Salicylicum acidicum, Silicea.

Uses†

Uses†: For symptomatic treatment of ringing, buzzing, undesirable noises, and general discomfort in the ears.

† as per various homeopathic materia medicas. These uses have not been evaluated by the FD, and product has not been clinically tested.

Warngings

Warnings: For external use only. If symptoms persist or worsen, discontinue use immediately and consutle a healthcare professional. If pregnant or breastfeeding, as ka health professional before use. Keep this and all medication out of reach of children. Avoid using near eyes or mouth. If swallowed, get medical help or contact a Poison Control Center immediately.

Discontinue sue if irritation or reaction occurs.

Directions

Directions: Shake well before using. Use at firest sign of symptoms. Dispense a small amount into hands. Massage gently onto cartilage of ourter ear canal and outer nostrils. Inhale deeply and slowly maintaining stillness. Repeat as needed.

FOR EXTERNAL USE ONLY

Keep carton for additional drug facts and information.

Tamper resistant for your protection.

Use only if safety seal is intact.

Inactive Ingredients

Inactive Ingredients: Grapeseed oil, ginger essential oil, cypress essential oil, grapefruit essential oil, lemon essential oil.

KEEP OUT OF REACH OF CHILDREN

Keep this and all medication out of reach of children.

PREGNANCY OR BREAST FEEDING

If pregnant or breastfeeding, ask a health professional before use.

PURPOSE

Temporarily soothes symptoms associated with ringing in the ears.